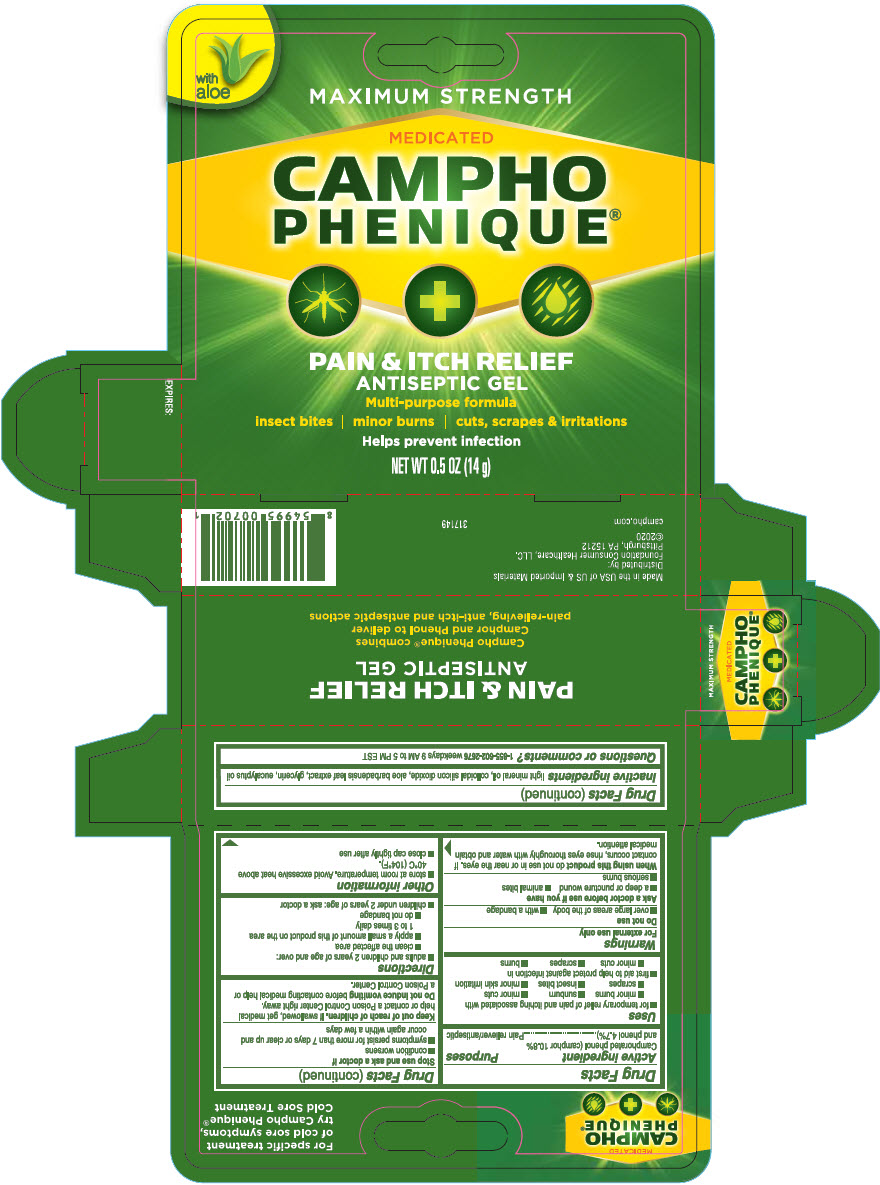 DRUG LABEL: Campho-Phenique
NDC: 69536-109 | Form: GEL
Manufacturer: Foundation Consumer Healthcare
Category: otc | Type: HUMAN OTC DRUG LABEL
Date: 20241202

ACTIVE INGREDIENTS: CAMPHOR (SYNTHETIC) 10.8 g/100 g; PHENOL 4.7 g/100 g
INACTIVE INGREDIENTS: SILICON DIOXIDE; EUCALYPTUS OIL; GLYCERIN; LIGHT MINERAL OIL; ALOE VERA LEAF

Campho-Phenique®
Antiseptic Gel

Drug Facts

Active ingredient

Camphorated phenol (camphor 10.8% and phenol 4.7%)

Purposes

Pain reliever/antiseptic

Uses

- for temporary relief of pain and itching associated with
  - minor burns
  - sunburn
  - minor cuts
  - scrapes
  - insect bites
  - minor skin irritation
- first aid to help protect against infection in
  - minor cuts
  - scrapes
  - burns

Warnings

For external use only

Do not use

- over large areas of the body
- with a bandage

Ask a doctor before use if you have

- a deep or puncture wound
- animal bites
- serious burns

WHEN USING

When using this productdo not use in or near the eyes. If contact occurs, rinse eyes thoroughly with water and obtain medical attention.

Stop use and ask a doctor if

- condition worsens
- symptoms persist for more than 7 days or clear up and occur again within a few days

Keep out of reach of children.If swallowed, get medical help or contact a Poison Control Center right away.

Do not induce vomitingbefore contacting medical help or a Poison Control Center.

Directions

- adults and children 2 years of age and over:
  - clean the affected area
  - apply a small amount of this product on the area 1 to 3 times daily
  - do not bandage
- children under 2 years of age: ask a doctor

Other information

- store at room temperature. Avoid excessive heat above 40°C (104°F).
- close cap tightly after use

Inactive ingredients

light mineral oil, colloidal silicon dioxide, aloe barbadensis leaf extract, glycerin, eucalyptus oil

Questions or comments?

1-855-602-2676weekdays 9 AM to 5 PM EST

Distributed by:
Foundation Consumer Healthcare, LLC.
Pittsburgh, PA 15212

PRINCIPAL DISPLAY PANEL - 14 g Tube Carton

with
aloe

MAXIMUM STRENGTH

MEDICATED
CAMPHO
PHENIQUE®

PAIN & ITCH RELIEF
ANTISEPTIC GEL

Multi-purpose formula

insect bites | minor burns | cuts, scrapes & irritations

Helps prevent infection

NET WT 0.5 OZ (14 g)